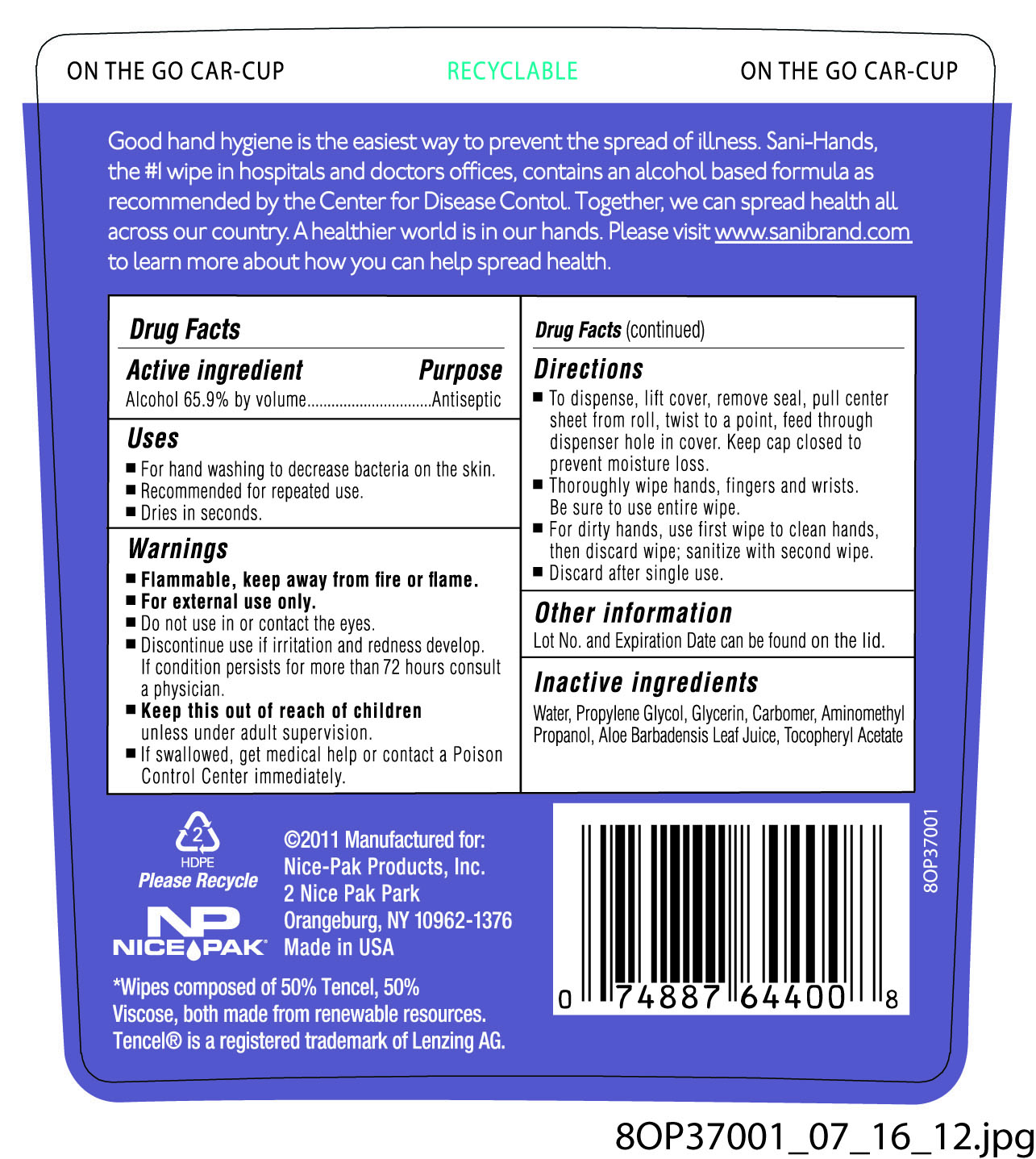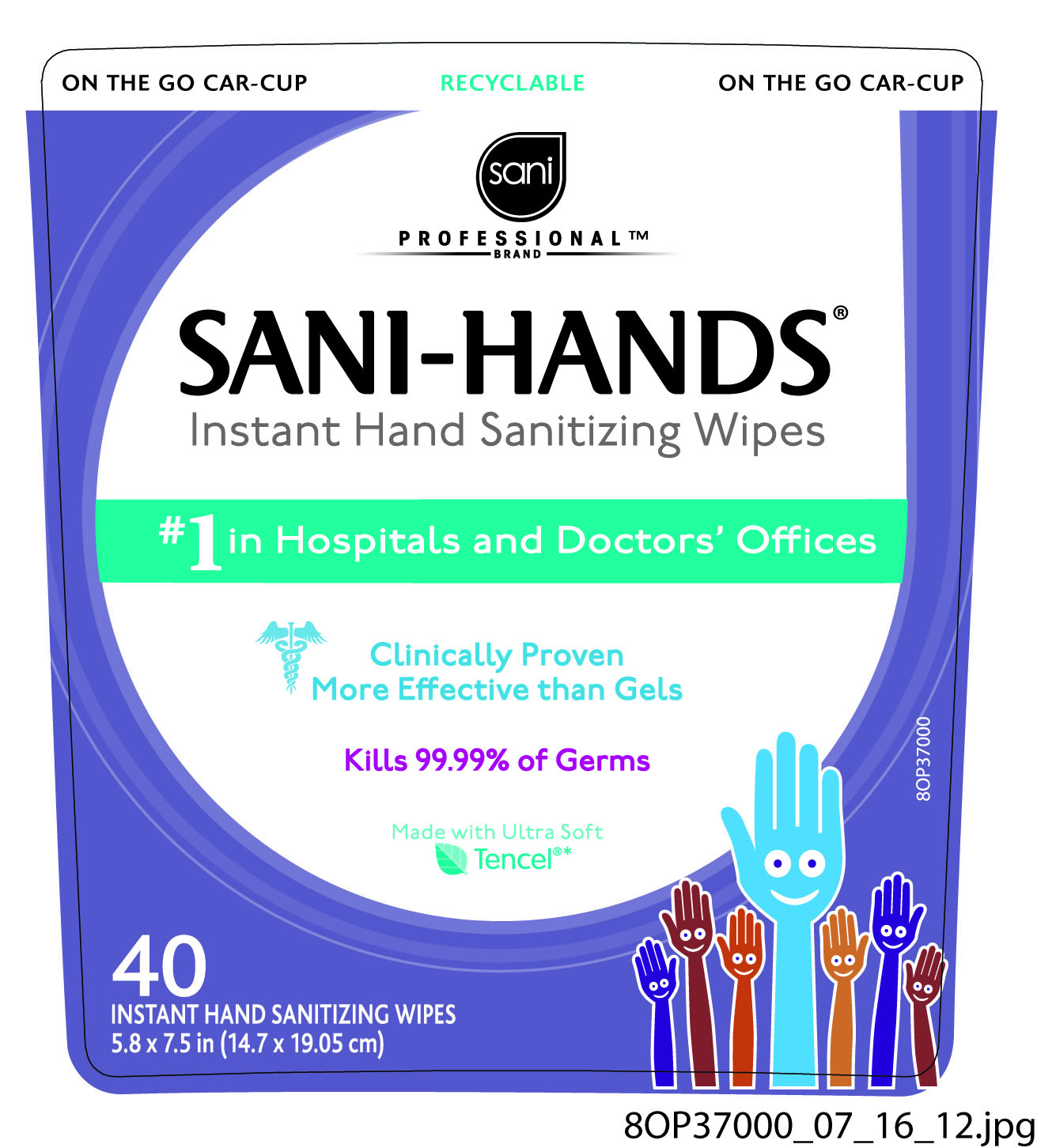 DRUG LABEL: Sani Professional Brand Sani-HandsInstant Hand Sani
NDC: 10819-5812 | Form: CLOTH
Manufacturer: Professional Disposables International, Inc.
Category: otc | Type: HUMAN OTC DRUG LABEL
Date: 20120814

ACTIVE INGREDIENTS: Alcohol 0.659 mL/1 mL
INACTIVE INGREDIENTS: WATER; PROPYLENE GLYCOL; GLYCERIN; CARBOMER HOMOPOLYMER TYPE C; AMINOMETHYL PROPANEDIOL; ALOE VERA LEAF; ALPHA-TOCOPHEROL ACETATE

SANI PROFESSIONAL SANI-HANDS INSTANT HAND SANITIZING WIPES

Uses

- For hand washing to decrease bacteria on the skin.
- Recommended for repeated use.
- Dries in seconds

Warnings

- Flammable, keep away from fire or flame.
- For external use only.
- Do not use in or contact the eyes.
- Discontinue use if irritation and redness develop. If condition persist for more than 72 hours consult a physician.
- If swallowed, get medical help or contact a Poison Control Center immediately.

KEEP OUT OF REACH OF CHILDREN

- Keep this out of reach of children unless under adult supervision.

Directions

- To dispense, lift cover, remove seal, pull center sheet from roll, twist to a point and feed through dispenser hole in cover. Keep cap closed to prevent moisture loss.
- Thoroughly wipe hands, fingers, and wrists. Be sure to use entire wipe.
- For dirty hands, use first wipe to clean hands, then discard wipe; sanitize with second wipe.
- Discard after single use.

Other information

Lot No. and Expiration Date can be found on the lid.

Dosage

For dirty hands, use first wipe to clean hands, then discard wipe; sanitize with second wipe. Discard after single use.

Inactive ingredients

Water, Propylene Glycol, Glycerin, Carbomer, Aminometyl Propanol, Aloe Barbadensis Leaf Juice, Tocopheryl Acetate

Good hand hygiene is the easiest way to prevent the spread of illness. Sani-Hands, the #1 wipe in hospitals and doctors offices, contains an alcohol based formula as recommended by the Center for Disease Control. Together, we can spread health all accross our country. A healthier world is in our hands. Please visit www.sanibrand.com to learn more about how you can help spread health.

(C) 2011 Manufactured for: Nice-Pak Products, Inc.
2 Nice-Pak Park, Orangeburg, NY 10962-1376 Made in USA

*Wipes composed of 50% Tencel, 50% Viscose, both made from renewable resources.

Tencel(R) is a registered trademark of Lenzing AG.

Principal Display Panel - 40 Count Canister

Sani
Professional(TM)
Brand
SANI-HANDS(R)
Instant Hand Sanitizing Wipes
#1 in Hospitals and Doctors' Offices
Clinically Proven More Effective than Gels
Kills 99.99% of Germs
Made with Ultra Soft TENCEL(R)*

40
INSTANT HAND SANITIZING WIPES
5.8 x 7.5 in (14.7 x 19.05 cm)

Front Canister Label
Back Canister Label

Active ingredient

Alcohol 65.9% by volume

Purpose

Antiseptic